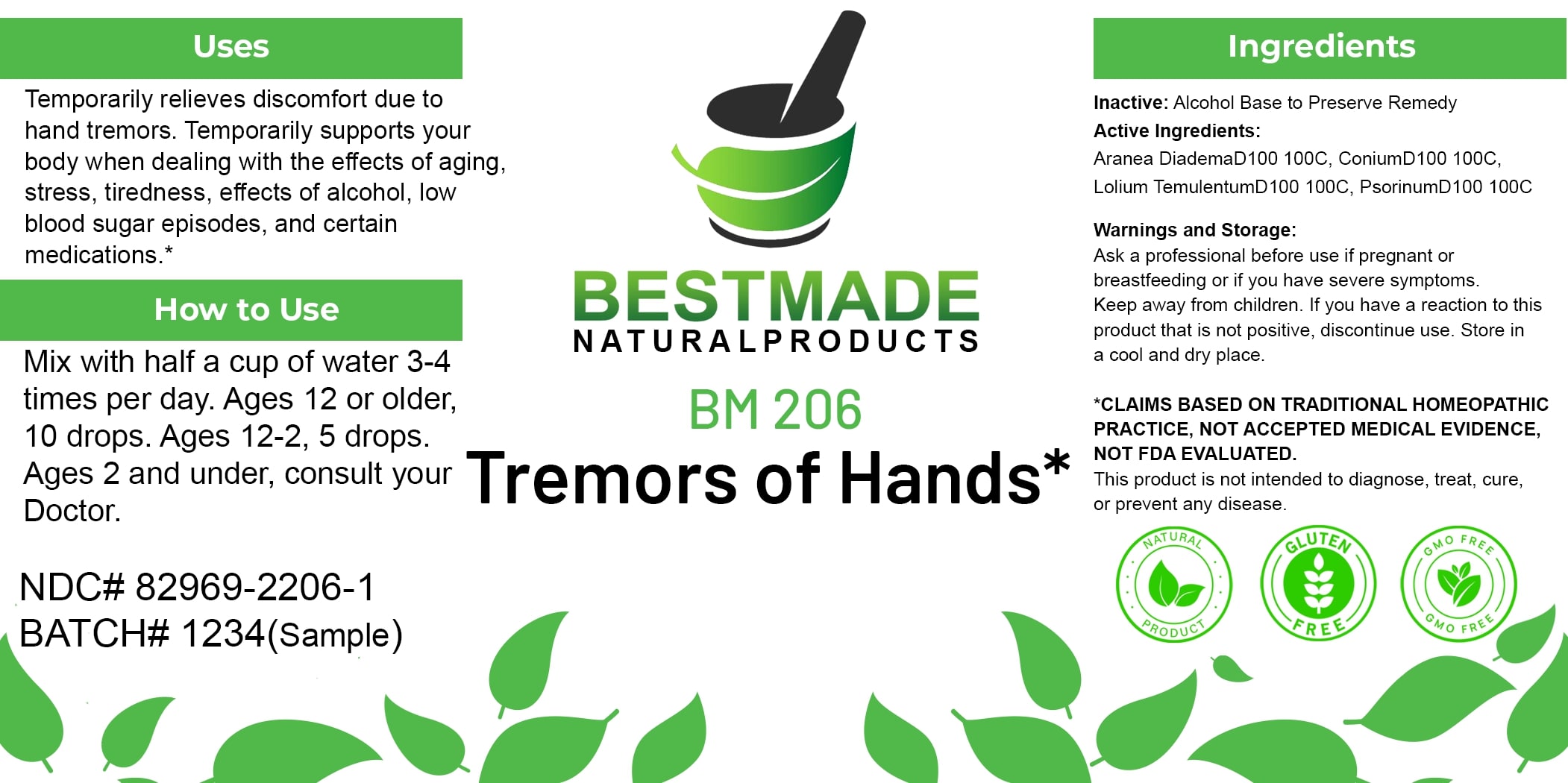 DRUG LABEL: Bestmade Natural Products BM206
NDC: 82969-2206 | Form: LIQUID
Manufacturer: Bestmade Natural Products
Category: homeopathic | Type: HUMAN OTC DRUG LABEL
Date: 20250326

ACTIVE INGREDIENTS: ARANEUS DIADEMATUS 100 [hp_C]/100 [hp_C]; CONIUM MACULATUM FLOWERING TOP 100 [hp_C]/100 [hp_C]; LOLIUM TEMULENTUM TOP 100 [hp_C]/100 [hp_C]; SCABIES LESION LYSATE (HUMAN) 100 [hp_C]/100 [hp_C]
INACTIVE INGREDIENTS: ALCOHOL 100 [hp_C]/100 [hp_C]

BM206

DOSAGE AND ADMINISTRATION

How to Use

Mix with half a cup of water 3-4 times per day. Ages 12 or older, 10 drops. Ages 12-2, 5 drops. Ages 2 and under, consult your Doctor.

Uses

Temporarily relieves discomfort due to hand tremors. Temporarily supports your body when dealing with the effects of aging, stress, tiredness, effects of alcohol, low blood sugar episodes, and certain medications.*

*CLAIMS BASED ON TRADITIONAL HOMEOPATHIC PRACTICE, NOT ACCEPTED MEDICAL EVIDENCE, NOT FDA EVALUATED.

This product is not intended to diagnose, treat, cure, or prevent any disease.

Uses

Temporarily relieves discomfort due to hand tremors. Temporarily supports your body when dealing with the effects of aging, stress, tiredness, effects of alcohol, low blood sugar episodes, and certain medications.*

*CLAIMS BASED ON TRADITIONAL HOMEOPATHIC PRACTICE, NOT ACCEPTED MEDICAL EVIDENCE, NOT FDA EVALUATED.

This product is not intended to diagnose, treat, cure, or prevent any disease.

INACTIVE INGREDIENT

Ingredients

Inactive: Alcohol Base to Preserve Remedy

ACTIVE INGREDIENT

Active Ingredients: Aranea DiademaD100+100C, ConiumD100+100C (Conium Maculatum), Lolium TemulentumD100+100C(Cockle), PsorinumD100+100C

KEEP OUT OF REACH OF CHILDREN

Warnings and Storage:

Ask a professional before use if pregnant or breastfeeding or if you have severe symptoms. Keep away from children. If you have a reaction to this product that is not positive, discontinue use. Store in a cool and dry place.

Warnings and Storage:

Ask a professional before use if pregnant or breastfeeding or if you have severe symptoms. Keep away from children. If you have a reaction to this product that is not positive, discontinue use. Store in a cool and dry place.

*CLAIMS BASED ON TRADITIONAL HOMEOPATHIC PRACTICE, NOT ACCEPTED MEDICAL EVIDENCE, NOT FDA EVALUATED.

This product is not intended to diagnose, treat, cure, or prevent any disease.

Entire package label